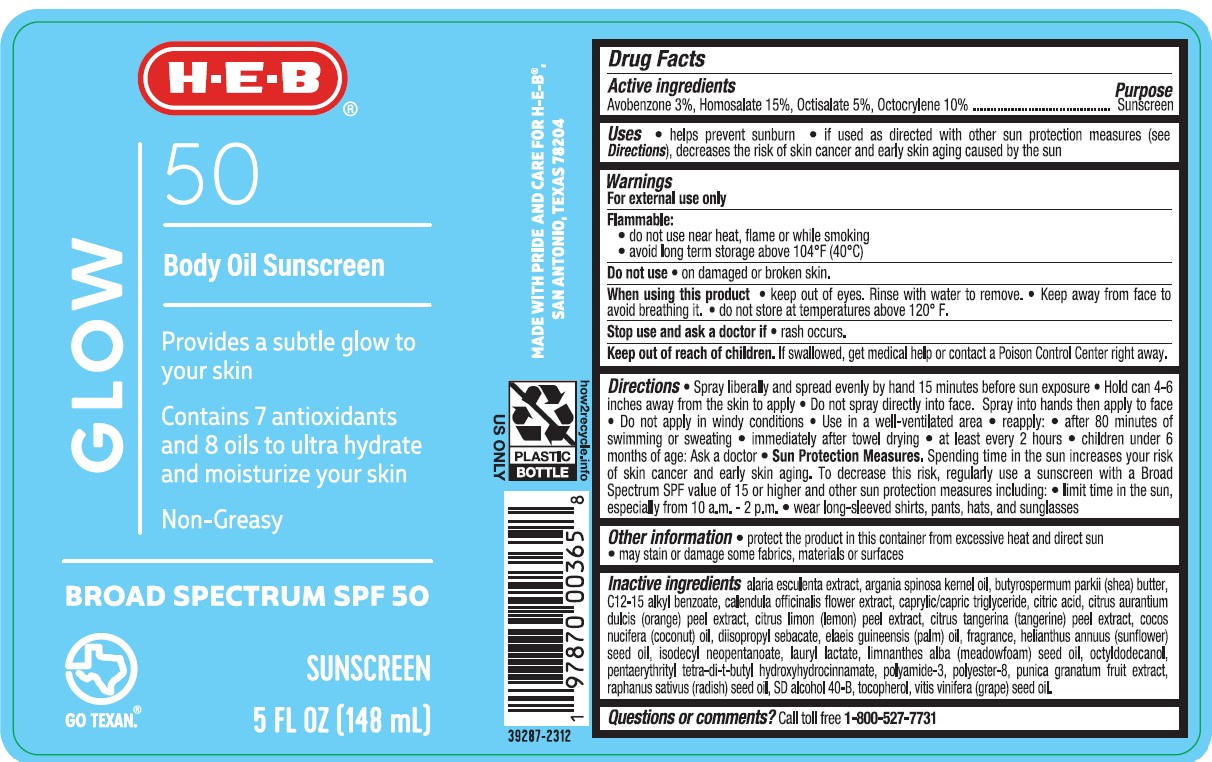 DRUG LABEL: HEB 50 Glow Body Oil Sunscreen
NDC: 37808-159 | Form: SPRAY
Manufacturer: H.E.B.
Category: otc | Type: HUMAN OTC DRUG LABEL
Date: 20250326

ACTIVE INGREDIENTS: AVOBENZONE 30 mg/1 mL; HOMOSALATE 150 mg/1 mL; OCTISALATE 50 mg/1 mL; OCTOCRYLENE 100 mg/1 mL
INACTIVE INGREDIENTS: RADISH; TANGERINE PEEL; ALARIA ESCULENTA; PALM OIL; ALCOHOL; POLYESTER-8 (1400 MW, CYANODIPHENYLPROPENOYL CAPPED); .ALPHA.-TOCOPHEROL, DL-; MEDIUM-CHAIN TRIGLYCERIDES; OCTYLDODECANOL; DIISOPROPYL SEBACATE; ISODECYL NEOPENTANOATE; LAURYL LACTATE; ANHYDROUS CITRIC ACID; PENTAERYTHRITOL TETRAKIS(3-(3,5-DI-TERT-BUTYL-4-HYDROXYPHENYL)PROPIONATE); POMEGRANATE; ORANGE PEEL; CALENDULA OFFICINALIS FLOWER; ARGAN OIL; SHEA BUTTER; SUNFLOWER OIL; MEADOWFOAM SEED OIL; GRAPE SEED OIL; COCONUT OIL; ALKYL (C12-15) BENZOATE; POLYAMIDE-3 (30000 MW); LEMON PEEL

HEB 50 Glow Body Oil Sunscreen

Active ingredients

Avobenzone 3.0%, Homosalate 15.0%, Octisalate 5.0%, Octocrylene 10.0%

Purpose

Sunscreen

Uses

- helps prevent sunburn
- if used as directed with other sun protection measures (see Directions), decreases the risk of skin cancer and early skin aging caused by the sun

Warnings

For external use only

FLAMMABLE:

• do not use near heat, flame or while smoking
• avoid long term storage above 104°F (40°C)

Do not use

- on damaged or broken skin

When using this product

• keep out of eyes. Rinse with water to remove. • do not puncture or incinerate. Contents under pressure. • do not store at temperatures above 120° F.

Stop use and ask doctor

if rash occurs.

Keep out of reach of children.

If product is swallowed, get medical help or contact a Poison Control Center right away.

Directions

• apply liberally 15 minutes before sun exposure
• hold can 4-6 inches away from body, spray evenly to ensure complete coverage
• do not spray into face. Spray into hand and apply to face.
• use in well ventilated, but not windy areas
• reapply:
• after 80 minutes of swimming or sweating
• immediately after towel drying
• at least every 2 hours

- children under 6 months: Ask a doctor

- Sun Protection Measures. Spending time in the sun increases your risk of skin cancer and early skin aging. To decrease this risk, regularly use a sunscreen with a Broad Spectrum SPF value of 15 or higher and other sun protection measures including:

• limit time in the sun, especially from 10 a.m. - 2 p.m.
• wear long-sleeved shirts, pants, hats, and sunglasses

Inactive ingredients

CAPRYLIC/CAPRIC TRIGLYCERIDE, SD ALCOHOL 40-B, C12-15 ALKYL BENZOATE, POLYAMIDE-3, OCTYLDODECANOL, POLYESTER-8, DIISOPROPYL SEBACATE, ISODECYL NEOPENTANOATE, LAURYL LACTATE, PUNICA GRANATUM FRUIT EXTRACT, CITRUS AURANTIUM DULCIS (ORANGE) PEEL EXTRACT, CALENDULA OFFICINALIS FLOWER EXTRACT, CITRUS LIMON (LEMON) PEEL EXTRACT, CITRUS TANGERINA (TANGERINE) PEEL EXTRACT, ALARIA ESCULENTA EXTRACT, FRAGRANCE, ELAEIS GUINEENSIS (PALM) OIL, ARGANIA SPINOSA KERNEL OIL, BUTYROSPERMUM PARKII (SHEA) BUTTER, COCOS NUCIFERA (COCONUT) OIL, HELIANTHUS ANNUUS (SUNFLOWER) SEED OIL, LIMNATHES ALBA (MEADOWFOAM) SEED OIL, RAPHANUS SATIVUS (RADISH) SEED OIL, VITIS VINIFERA (GRAPE) SEED OIL, TOCOPHEROL, PENTAERYTHRITYL TETRA-DI-T-BUTYL HYDROXYHYDROCINNAMATE, CITRIC ACID

Other Information

• protect the product in this container from excessive heat and direct sun
• may stain or damage some fabrics, materials or surfaces